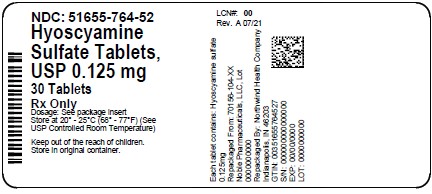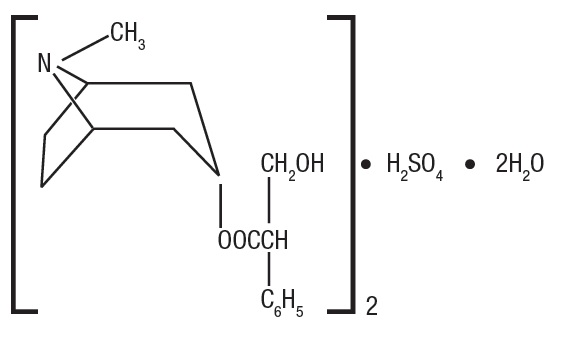 DRUG LABEL: Hyoscyamine Sulfate
NDC: 51655-764 | Form: TABLET
Manufacturer: Northwind Health Company, LLC
Category: prescription | Type: HUMAN PRESCRIPTION DRUG LABEL
Date: 20260101

ACTIVE INGREDIENTS: HYOSCYAMINE SULFATE 0.125 mg/1 1
INACTIVE INGREDIENTS: STARCH, CORN; LACTOSE MONOHYDRATE; MAGNESIUM STEARATE; MANNITOL; STEARIC ACID; FD&C BLUE NO. 1

Hyoscyamine Sulfate Tablets USP, 0.125 mg
Rx Only

DESCRIPTION

Hyoscyamine Sulfate Tablets, USP contain 0.125 mg hyoscyamine sulfate formulated for oral administration.

Hyoscyamine sulfate is one of the principal anticholinergic/antispasmodic components of belladonna alkaloids. The empirical formula is (C17H23NO3)2•H2SO4•2H2O and the molecular weight is 712.85. Chemically, it is benzeneacetic acid, α-(hydroxymethyl)-, 8-methyl-8-azabicyclo [3.2.1] oct-3-yl ester, [3(S)-endo]-, sulfate (2:1), dihydrate with the following structure:

Each tablet also contains as inactive ingredients: corn starch, lactose monohydrate, magnesium stearate, mannitol, stearic acid, and FD&C blue #1.

CLINICAL PHARMACOLOGY

Hyoscyamine sulfate inhibits specifically the actions of acetylcholine on structures innervated by postganglionic cholinergic nerves and on smooth muscles that respond to acetylcholine but lack cholinergic innervation. These peripheral cholinergic receptors are present in the autonomic effector cells of the smooth muscle, cardiac muscle, the sinoatrial node, the atrioventricular node and the exocrine glands. At therapeutic doses, it is completely devoid of any action on the autonomic ganglia. Hyoscyamine sulfate inhibits gastrointestinal propulsive motility and decreases gastric acid secretion. Hyoscyamine sulfate also controls excessive pharyngeal, tracheal and bronchial secretions.

Hyoscyamine sulfate is absorbed totally and completely by oral administration. Once absorbed, hyoscyamine sulfate disappears rapidly from the blood and is distributed throughout the entire body. The half-life of hyoscyamine sulfate is 2 to 3 1/2 hours. Hyoscyamine sulfate is partly hydrolyzed to tropic acid and tropine but the majority of the drug is excreted in the urine unchanged within the first 12 hours. Only traces of this drug are found in breast milk. Hyoscyamine sulfate passes the blood brain barrier and the placental barrier.

INDICATIONS AND USAGE

Hyoscyamine Sulfate Tablets, USP are effective as adjunctive therapy in the treatment of peptic ulcer. They can also be used to control gastric secretions, visceral spasm and hypermotility in spastic colitis, spastic bladder, cystitis, pylorospasm and associated abdominal cramps. May be used in functional intestinal disorders to reduce symptoms such as those seen in mild dysenteries, diverticulitis and acute enterocolitis. For use as adjunctive therapy in the treatment of irritable bowel syndrome (irritable colon, spastic colon, mucous colitis) and functional gastrointestinal disorders. Also used as adjunctive therapy in the treatment of neurogenic bladder and neurogenic bowel disturbances (including the splenic flexure syndrome and neurogenic colon). Hyoscyamine Sulfate Tablets, USP are indicated along with morphine or other narcotics in symptomatic relief of biliary and renal colic; as a “drying agent” in the relief of symptoms of acute rhinitis; in the therapy of parkinsonism to reduce rigidity and tremors and to control associated sialorrhea and hyperhidrosis. May be used in the therapy of poisoning by anticholinesterase agents.

CONTRAINDICATIONS

Glaucoma; obstructive uropathy (for example, bladder neck obstruction due to prostatic hypertrophy); obstructive disease of the gastrointestinal tract (as in achalasia, pyloroduodenal stenosis); paralytic ileus, intestinal atony of elderly or debilitated patients; unstable cardiovascular status in acute hemorrhage; severe ulcerative colitis; toxic megacolon complicating ulcerative colitis; myasthenia gravis.

WARNINGS

In the presence of high environmental temperature, heat prostration can occur with drug use (fever and heat stroke due to decreased sweating). Diarrhea may be an early symptom of incomplete intestinal obstruction, especially in patients with ileostomy or colostomy. In this instance, treatment with this drug would be inappropriate and possibly harmful. Like other anticholinergic agents, hyoscyamine sulfate may produce drowsiness, dizziness or blurred vision. In this event, the patient should be warned not to engage in activities requiring mental alertness such as operating a motor vehicle or other machinery or to perform hazardous work while taking this drug.

Psychosis has been reported in sensitive individuals given anticholinergic drugs including hyoscyamine sulfate. CNS signs and symptoms include confusion, disorientation, short-term memory loss, hallucinations, dysarthria, ataxia, coma, euphoria, anxiety, decreased anxiety, fatigue, insomnia, agitation and mannerisms and inappropriate affect. These CNS signs and symptoms usually resolve within 12 to 48 hours after discontinuation of the drug.

PRECAUTIONS

General:

Use with caution in patients with: autonomic neuropathy, hyperthyroidism, coronary heart disease, congestive heart failure, cardiac arrhythmias, hypertension and renal disease. Investigate any tachycardia before giving any anticholinergic drugs since they may increase the heart rate. Use with caution in patients with hiatal hernia associated with reflux esophagitis.

Information for Patients:

Like other anticholinergic agents, hyoscyamine sulfate may produce drowsiness, dizziness or blurred vision. In this event, the patient should be warned not to engage in activities requiring mental alertness such as operating a motor vehicle or other machinery or to perform hazardous work while taking this drug.

Use of hyoscyamine sulfate may decrease sweating resulting in heat prostration, fever or heat stroke; febrile patients or those who may be exposed to elevated environmental temperatures should use caution.

Drug Interactions:

Additive adverse effects resulting from cholinergic blockade may occur when hyoscyamine sulfate is administered concomitantly with other antimuscarinics, amantadine, haloperidol, phenothiazines, monoamine oxidase (MAO) inhibitors, tricyclic antidepressants or some antihistamines.

Antacids may interfere with the absorption of hyoscyamine sulfate. Administer hyoscyamine sulfate before meals; antacids after meals.

Carcinogenesis, Mutagenesis, Impairment of Fertility:

No long-term studies in animals have been performed to determine the carcinogenic, mutagenic or impairment of fertility potential of hyoscyamine sulfate; however, 40 years of marketing experience with hyoscyamine sulfate shows no demonstrable evidence of a problem.

Pregnancy-Pregnancy Category C:

Animal reproduction studies have not been conducted with hyoscyamine sulfate. It is also not known whether hyoscyamine sulfate can cause fetal harm when administered to a pregnant woman or can affect reproduction capacity. Hyoscyamine sulfate should be given to a pregnant woman only if clearly needed.

Nursing Mothers:

Hyoscyamine sulfate is excreted in human milk. Caution should be exercised when hyoscyamine sulfate are administered to a nursing woman.

Geriatric Use:

Reported clinical experience has not identified differences in safety between patients aged 65 and over and younger patients. In general, dose selection for an elderly patient should be cautious, usually starting at the low end of the dosing range, reflecting the greater frequency of decreased hepatic, renal, or cardiac function and of concomitant disease or other drug therapy.

This drug is known to be substantially excreted by the kidney, and the risk of toxic reactions to this drug may be greater in patients with impaired renal function. Because elderly patients are more likely to have decreased renal function, care should be taken in dose selection, and it may be useful to monitor renal function.

ADVERSE REACTIONS

The following adverse reactions have been reported for hyoscyamine sulfate and for pharmacologically similar drugs with anticholinergic/antispasmodic action. Adverse reactions may include dryness of the mouth; urinary hesitancy and retention; blurred vision; tachycardia; palpitations; mydriasis; cycloplegia; increased ocular tension; loss of taste; headache; nervousness; drowsiness; weakness; fatigue; dizziness; insomnia; nausea; vomiting; impotence; suppression of lactation; constipation; bloated feeling; abdominal pain; diarrhea; allergic reactions or drug idiosyncrasies; urticaria and other dermal manifestations; ataxia; speech disturbance; some degree of mental confusion and/or excitement (especially in elderly persons); short-term memory loss; hallucinations; and decreased sweating.

To report SUSPECTED ADVERSE REACTIONS, contact Noble Pharmaceuticals, LLC at 1-888-514-4727 or FDA at 1-800-FDA-1088 or www.fda.gov/medwatch.

OVERDOSAGE

The signs and symptoms of overdose are headache, nausea, vomiting, blurred vision, dilated pupils, hot dry skin, dizziness, dryness of the mouth, difficulty in swallowing and CNS stimulation.

Measures to be taken are immediate lavage of the stomach and injection of physostigmine 0.5 to 2 mg intravenously and repeated as necessary up to a total of 5 mg. Fever may be treated symptomatically (tepid water sponge baths, hypothermic blanket). Excitement to a degree which demands attention may be managed with sodium thiopental 2% solution given slowly intravenously or chloral hydrate (100-200 mL of a 2% solution) by rectal infusion. In the event of progression of the curare-like effect to paralysis of the respiratory muscles, artificial respiration should be instituted and maintained until effective respiratory action returns.

In rats, the LD50 for hyoscyamine is 375 mg/kg. Hyoscyamine sulfate is dialyzable.

DOSAGE AND ADMINISTRATION

Dosage may be adjusted according to the conditions and severity of symptoms.

Adults and pediatric patients 12 years of age and older: 1 to 2 tablets every four hours or as needed. Do not exceed 12 tablets in 24 hours.

Pediatric patients 2 to under 12 years of age: 1/2 to 1 tablet every four hours or as needed. Do not exceed 6 tablets in 24 hours.

HOW SUPPLIED

Hyoscyamine Sulfate Tablets, USP, 0.125 mg are light blue, round, biconvex tablets, debossed with “N” on one side and “104” on the other.

Bottles of 30 NDC 51655-764-52

Store at controlled room temperature 20C°-25°C (68F°-77°F); excursion permitted to 15C°-30°C (59F°-86°F) see USP controlled room temperature.

Dispense in tight, light-resistant containers as defined in USP/NF with a child-resistant closure.

KEEP THIS AND ALL DRUGS OUT OF THE REACH OF CHILDREN.

Marketed by:

Noble Pharmaceuticals, LLC
Cooper City, FL 33024

Iss. 09/18

PRINCIPAL DISPLAY PANEL

NDC: 51655-764-52